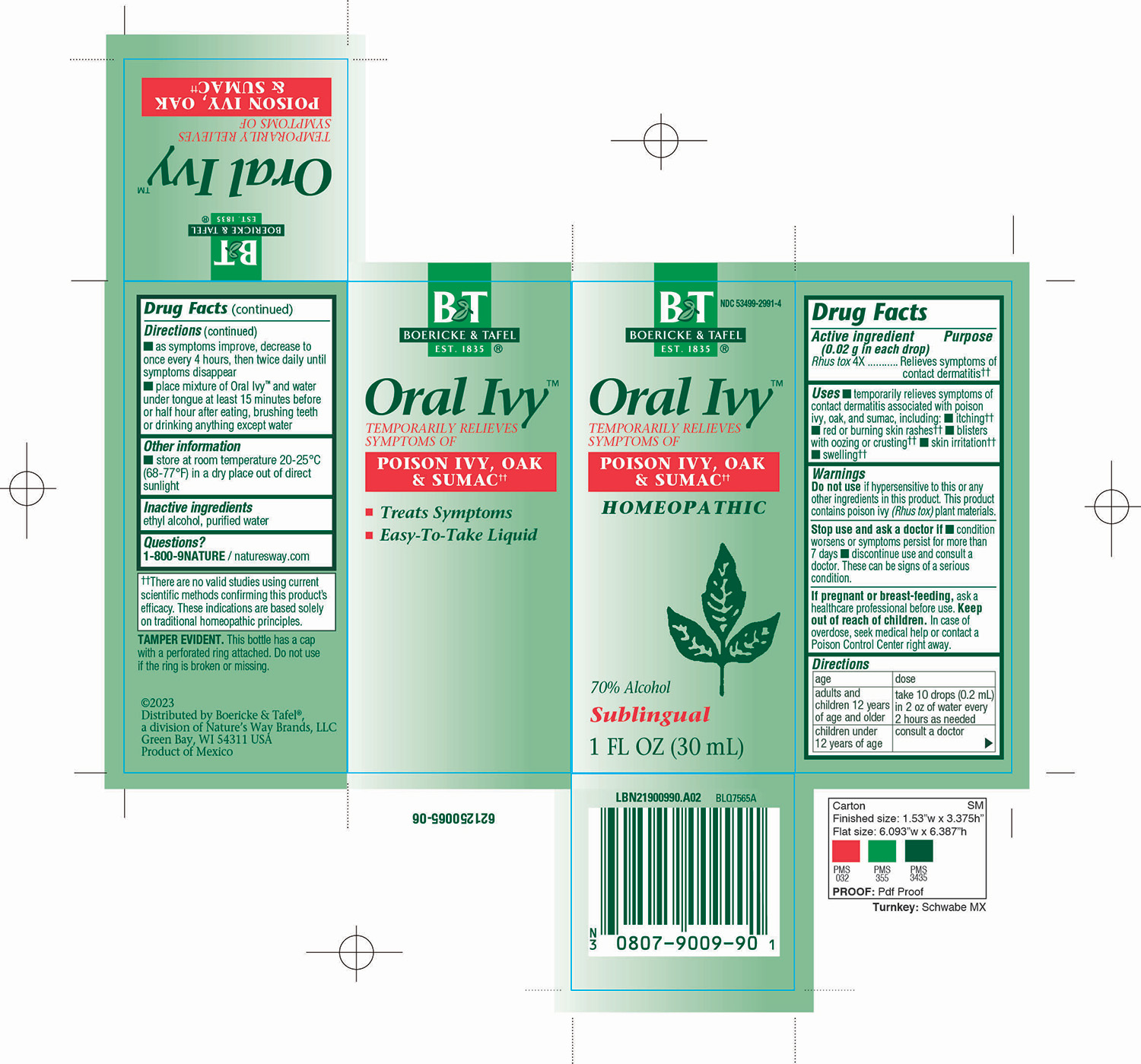 DRUG LABEL: Oral Ivy Liquid 
NDC: 68466-2015 | Form: LIQUID
Manufacturer: Schwabe Mexico, S.A. de C.V.
Category: homeopathic | Type: HUMAN OTC DRUG LABEL
Date: 20251124

ACTIVE INGREDIENTS: TOXICODENDRON PUBESCENS LEAF 4 [hp_X]/30 mL
INACTIVE INGREDIENTS: ALCOHOL; WATER

Oral Ivy (Rhus toxicodendron) Liquid

Active Ingredient

Rhus tox 4X

Inactive Ingredient

Ethyl Alcohol

Purified Water

Dosage & Adminstration

Directions

Adults and Children 12 years of age and older: Take 10 drops (0.2 ml) in 2 oz of water every 2 hours as needed.

Children under 12 years of age: Consult a doctor.

As symptoms improve, decrease to once every 4 hours, then twice daily until symptoms disappear.

Place mixture of Oral Ivy™ and water under tongue at least 15 minutes before or half hour after eating, brushing teeth, or drinking anything except water.

Purpose

Temporarily relieves symptoms of contact dermatitis associated with poison ivy, oak, and sumac, including: itching, red or burning skin rashes, blisters with oozing or crusting, skin irritation, and swelling.

Indications & Usage

Temporarily relieves symptoms of contact dermatitis associated with poison ivy, oak, and sumac, including: itching, red or burning skin rashes, blisters with oozing or crusting, skin irritation, and swelling.

Warnings

Do not use if hypersensitive to this or any other ingredients in this product.

This product contains poison ivy (Rhus tox) plant materials.

Stop Use

Stop use and ask a doctor if condition worsens or symptoms persist for more than 7 days.

Discontinue use and consult a doctor.

These can be signs of a serious condition.

Pregnancy or Breast Feeding

If pregnant or breast-feeding, ask a healthcare professional before use.

Keep Out of Reach of Children

Overdose

In case of overdose, seek medical help or contact a Poison Control Center right away.